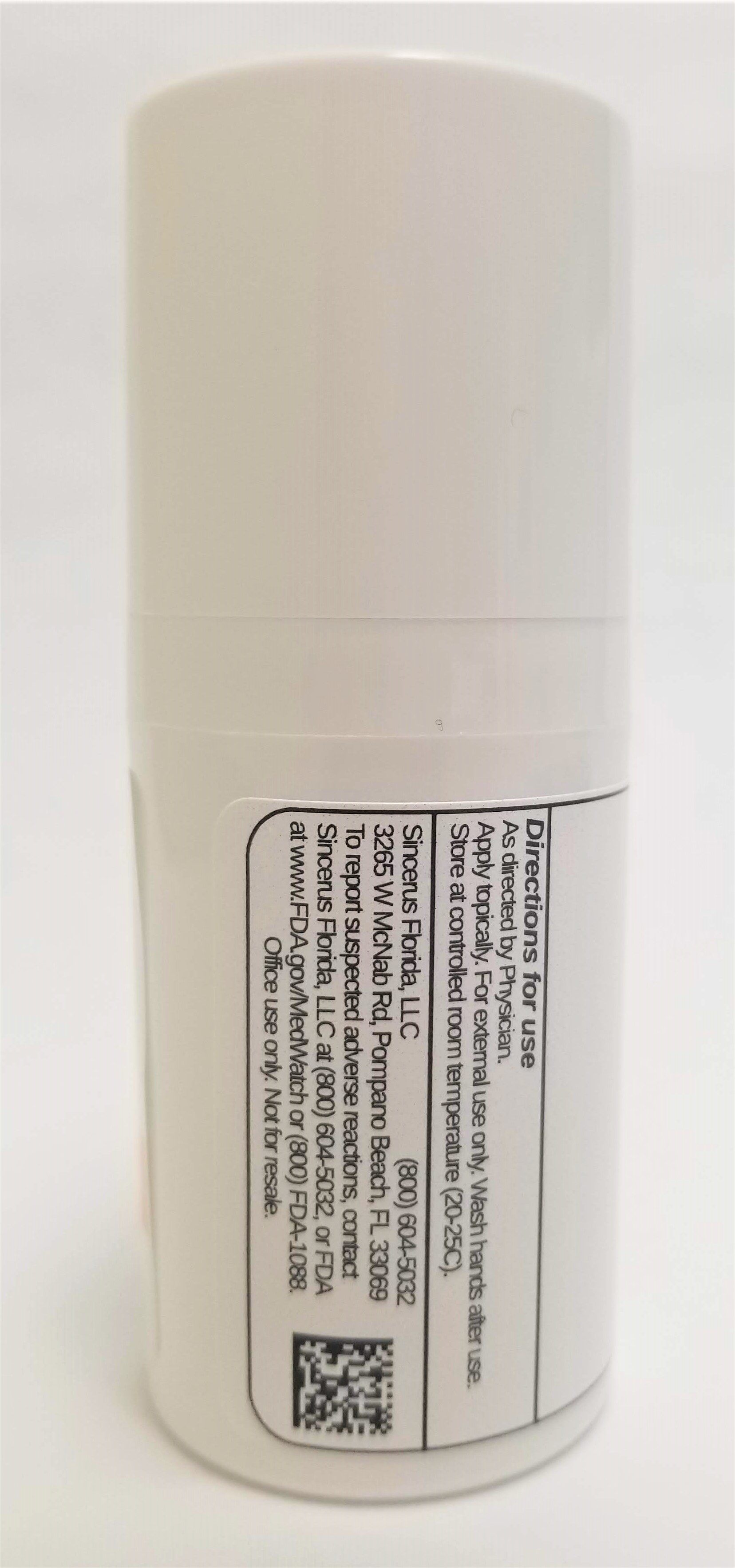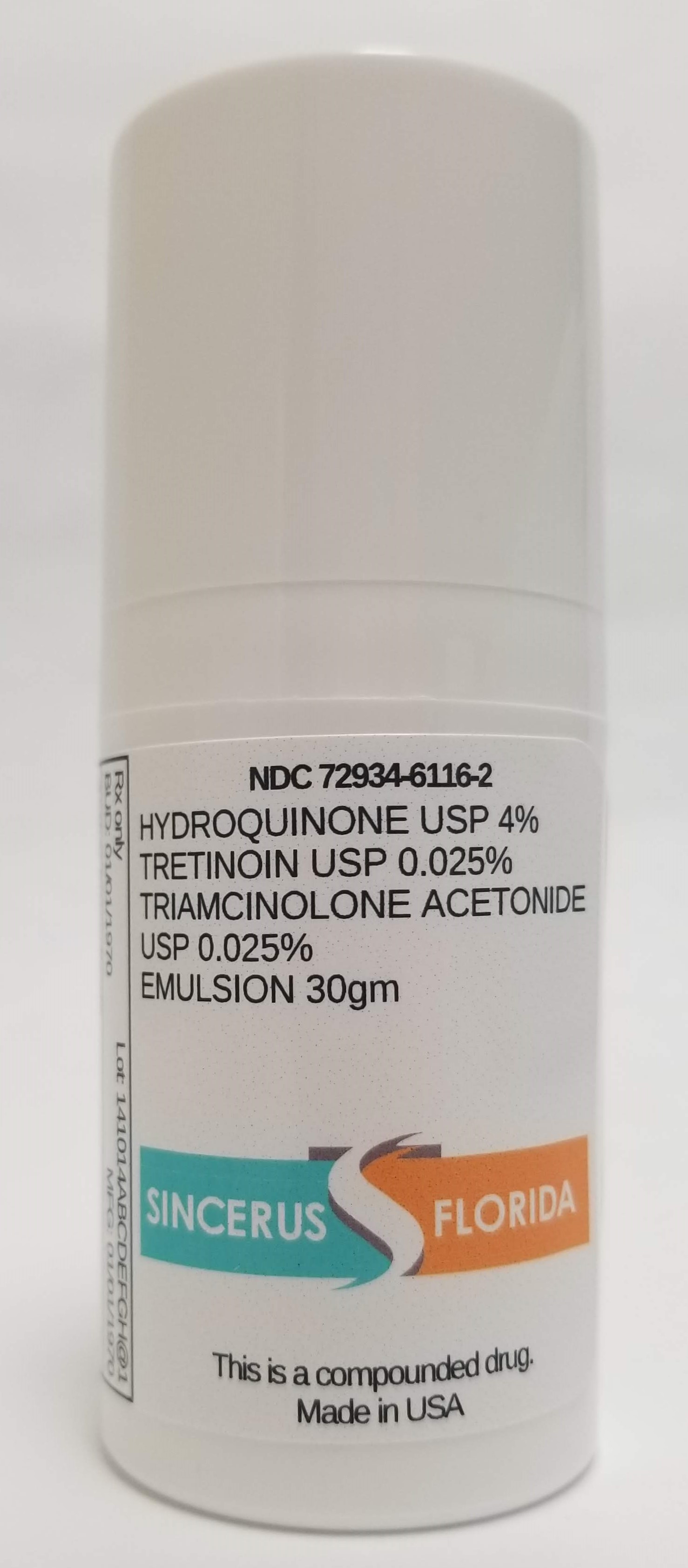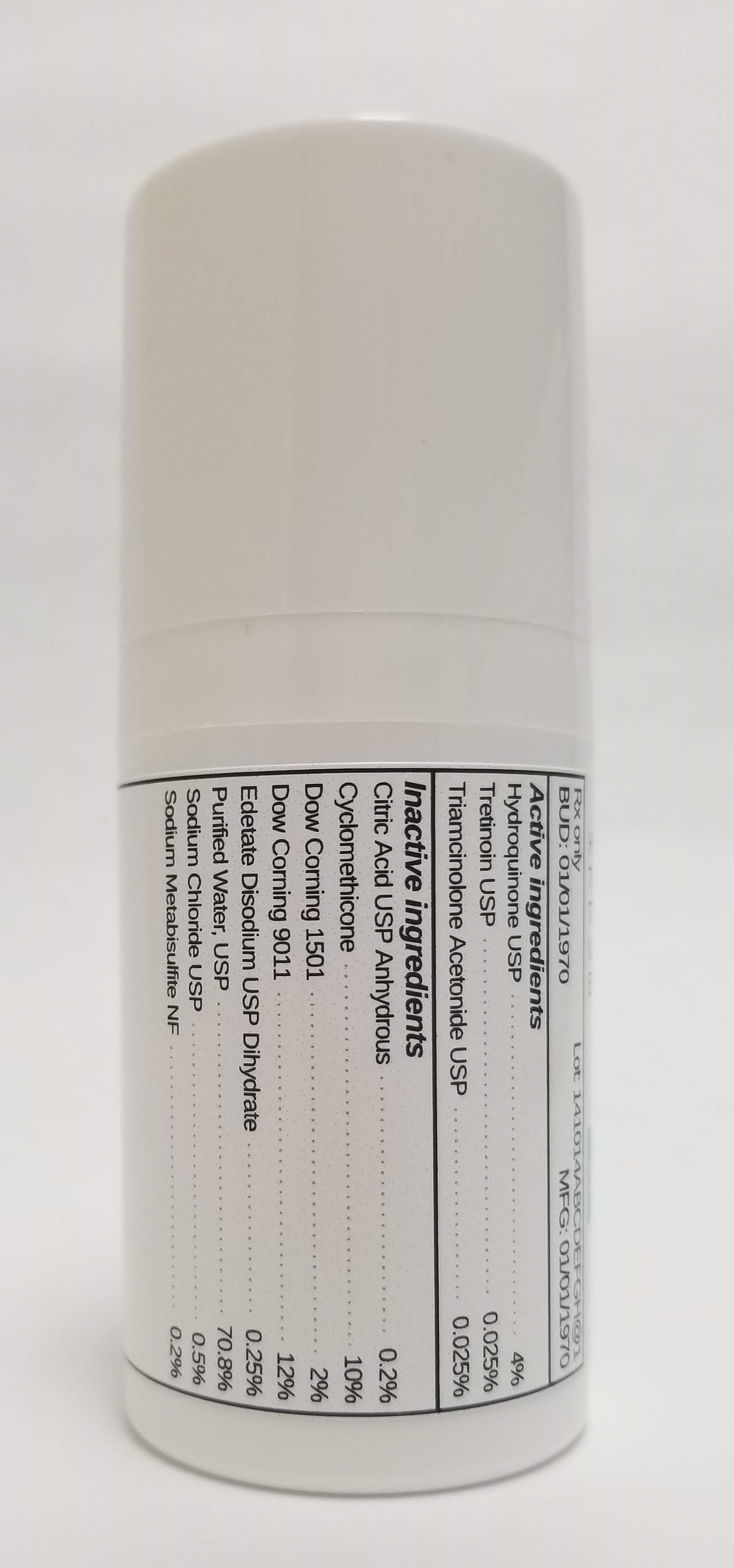 DRUG LABEL: HYDROQUINONE 4% / TRETINOIN 0.025% / TRIAMCINOLONE ACETONIDE 0.025%
NDC: 72934-6116 | Form: EMULSION
Manufacturer: Sincerus Florida, LLC
Category: prescription | Type: HUMAN PRESCRIPTION DRUG LABEL
Date: 20190520

ACTIVE INGREDIENTS: TRETINOIN 0.025 g/100 g; HYDROQUINONE 4 g/100 g; TRIAMCINOLONE ACETONIDE 0.025 g/100 g

HYDROQUINONE 4% / TRETINOIN 0.025% / TRIAMCINOLONE ACETONIDE 0.025%